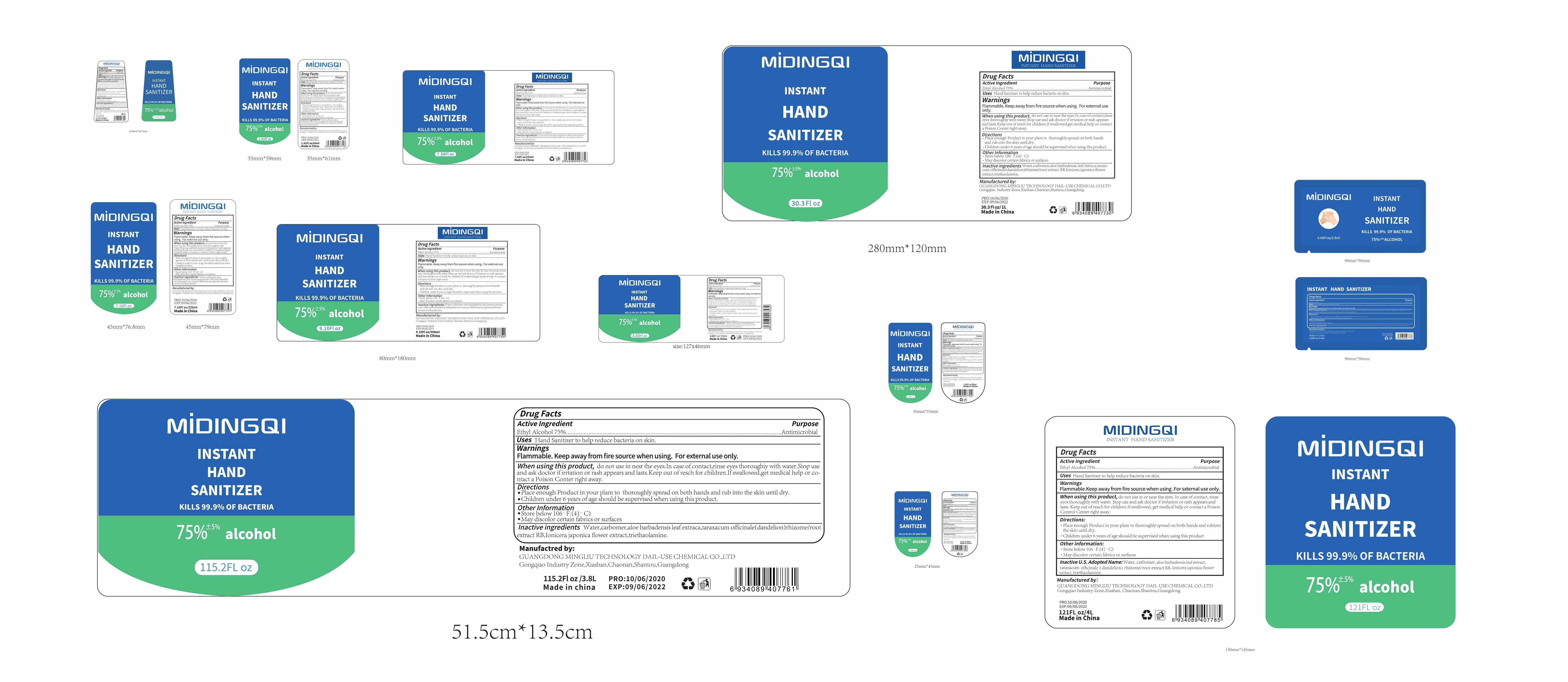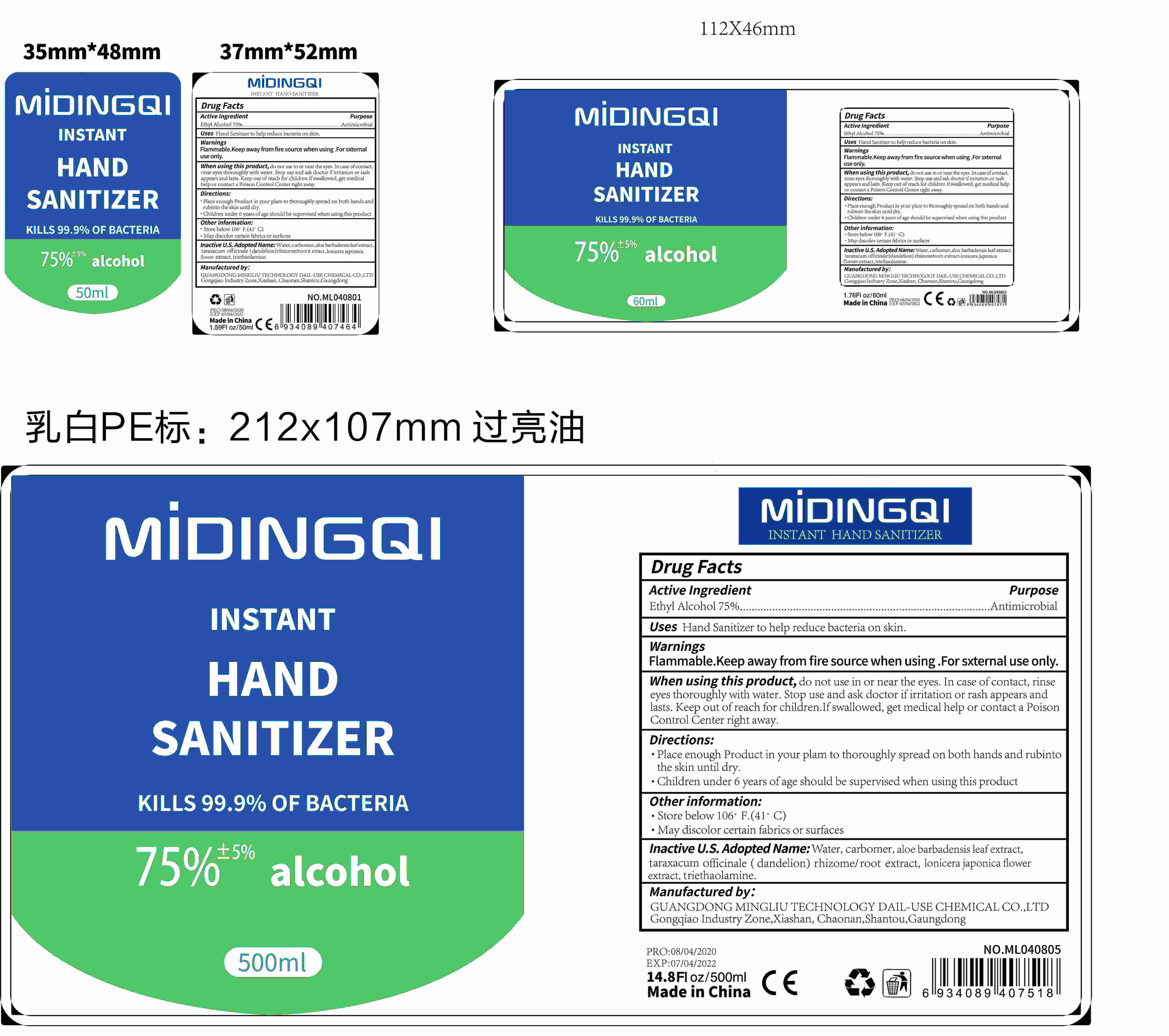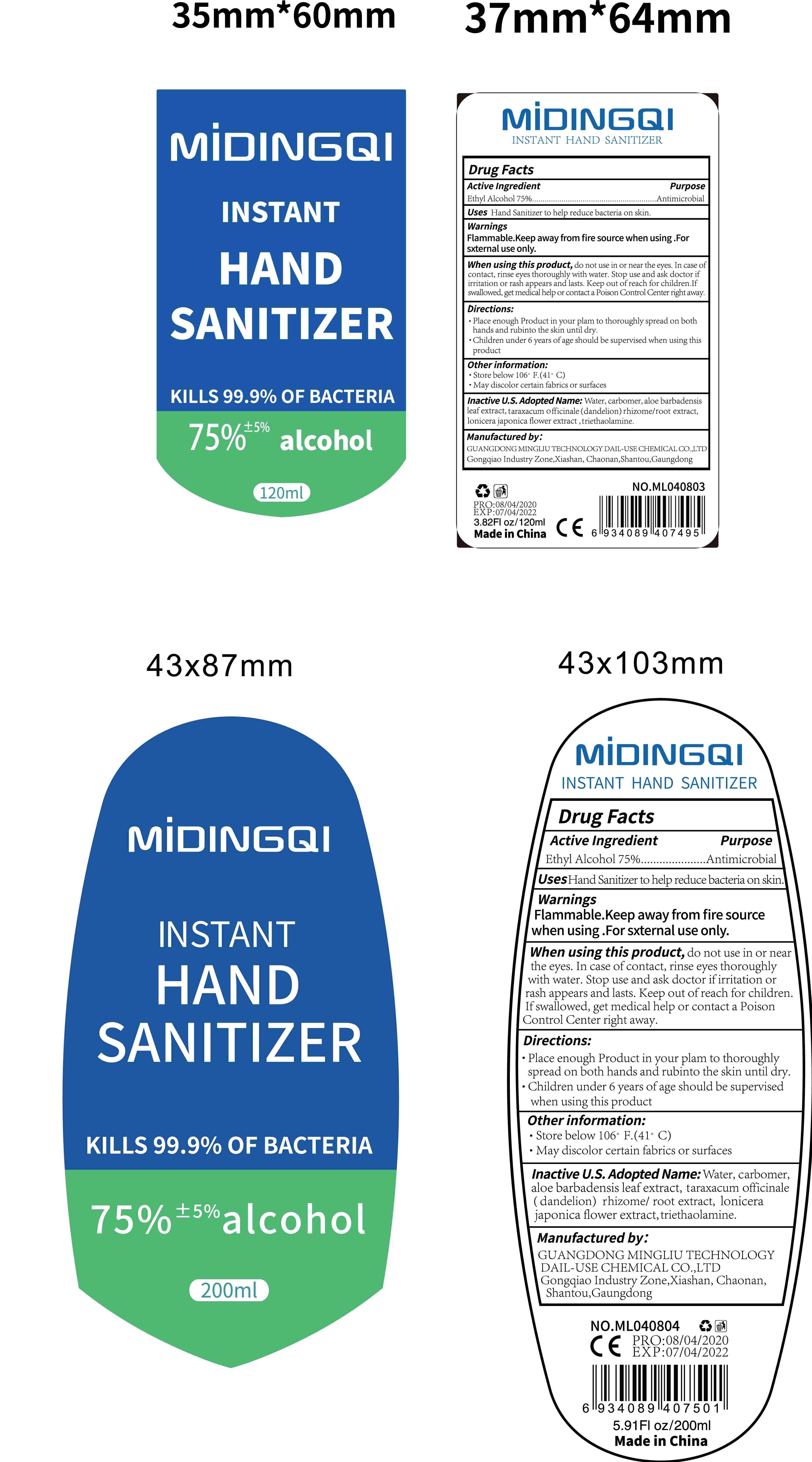 DRUG LABEL: Instant Hand Sanitizer
NDC: 75209-008 | Form: GEL
Manufacturer: GUANGDONG MINGLIU TECHNOLOGY DAIL-USE CHEMICAL CO., LTD.
Category: otc | Type: HUMAN OTC DRUG LABEL
Date: 20200608

ACTIVE INGREDIENTS: ALCOHOL 75 mL/100 mL
INACTIVE INGREDIENTS: TARAXACUM OFFICINALE ROOT; CARBOMER 934; ALOE; WATER; TROLAMINE; LONICERA JAPONICA FLOWER

Active Ingredient(s)

Ethyl Alcohol75% v/v. Purpose: Antimicrobial

Purpose

Antimicrobial

Use

Uses Hand Sanitizer to held reduce bacteria on skin

Warnings

Flammable. Keep away from fire source when using For sxternal use only.

- do not use in or near the eyes

When using this product, do not use in or near the eyes. In case of contact, rinseeyes thoroughly with water Stop use and ask doctor if irritation or rash appears andlasts. Keep out of reach for children. If swallowed, get medical help or contact a PoisonControl Center right away

Stop use and ask doctor if irritation or rash appedears anclasts.

Keep out of reach of children. If swallowed, get medical help or contact a Poison Control Center right away.

Directions

- Place enough Product in your plam to thoroughly spread on both hands and rubinto skin until dry.
  Children under 6 years of age should be supervised when using this product

Other information

- Store between 15-30C (59-86F)
- Avoid freezing and excessive heat above 40C (104F)

Inactive ingredients

Water, carbomer, aloe barbadensis leaf extract,taraxacum officinale(dandelion)rhizome/root extract, lonicera japonica flowerextract, triethanolamine